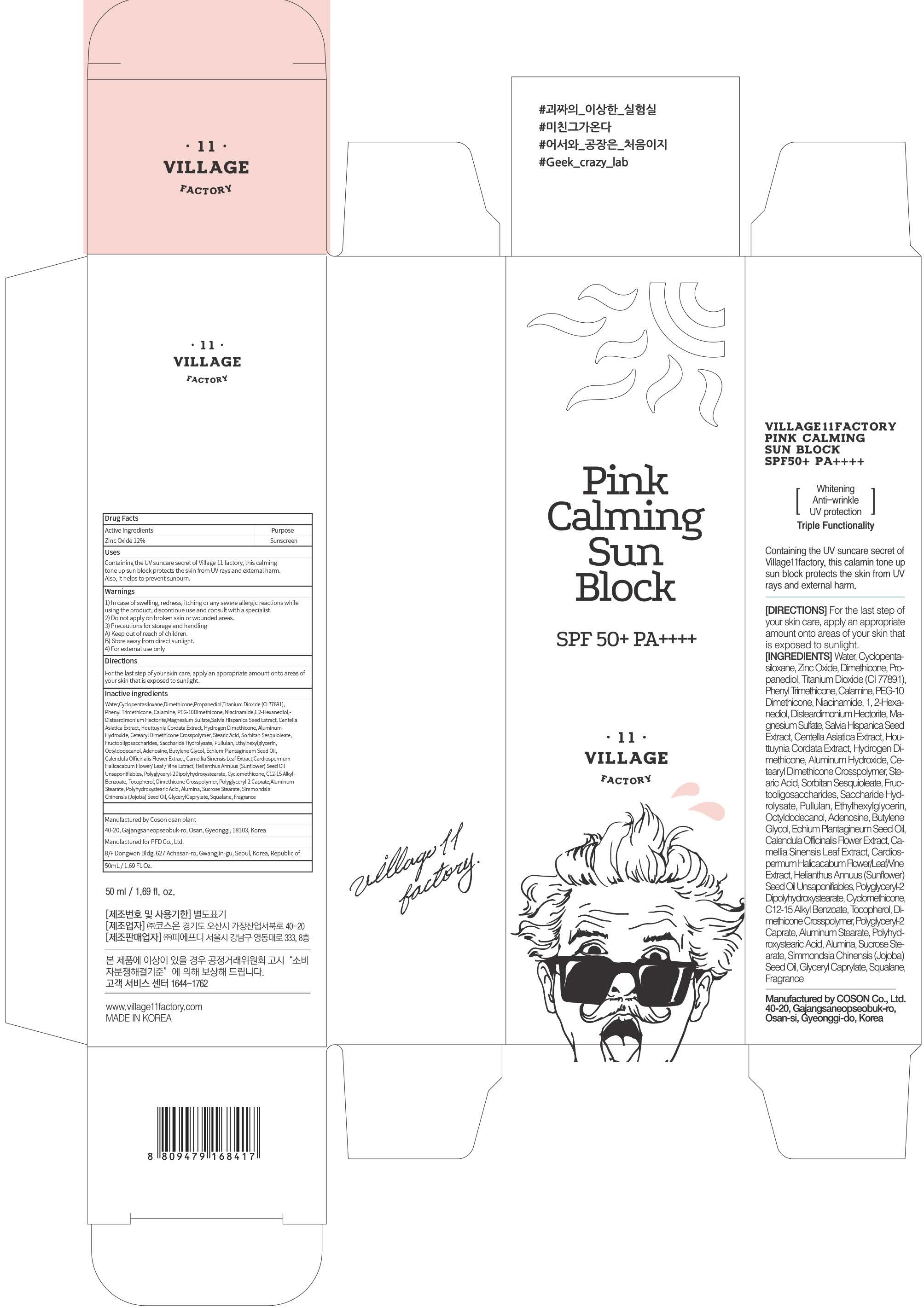 DRUG LABEL: VILLAGE11FACTORY PINK CALMING SUN BLOCK
NDC: 72470-030 | Form: CREAM
Manufacturer: PFD Co.,Ltd.
Category: otc | Type: HUMAN OTC DRUG LABEL
Date: 20180807

ACTIVE INGREDIENTS: Zinc Oxide 6.00 g/50 mL
INACTIVE INGREDIENTS: Water; Dimethicone

ACTIVE INGREDIENT

Active ingredients: Zinc Oxide 12%

INACTIVE INGREDIENT

Inactive ingredients:

Water,Cyclopentasiloxane,Dimethicone,Propanediol,Titanium Dioxide (CI 77891),Phenyl Trimethicone, Calamine, PEG-10Dimethicone, Niacinamide,1,2-Hexanediol, Disteardimonium Hectorite,Magnesium Sulfate,Salvia Hispanica Seed Extract, Centella Asiatica Extract, Houttuynia Cordata Extract, Hydrogen Dimethicone, Aluminum Hydroxide, Cetearyl Dimethicone Crosspolymer, Stearic Acid, Sorbitan Sesquioleate, Fructooligosaccharides, Saccharide Hydrolysate, Pullulan, Ethylhexylglycerin, Octyldodecanol,Adenosine, Butylene Glycol, Echium Plantagineum Seed Oil,Calendula Officinalis Flower Extract, Camellia Sinensis Leaf Extract,Cardiospermum Halicacabum Flower/ Leaf/Vine Extract, Helianthus Annuus (Sunflower) Seed Oil Unsaponifiables, Polyglyceryl-2Dipolyhydroxystearate, Cyclomethicone, C12-15 Alkyl Benzoate, Tocopherol, Dimethicone Crosspolymer, Polyglyceryl-2 Caprate,Aluminum Stearate, Polyhydroxystearic Acid, Alumina, Sucrose Stearate, Simmondsia Chinensis (Jojoba) Seed Oil, GlycerylCaprylate, Squalane, Fragrance

PURPOSE

Purpose: Sunscreen

WARNINGS

1) In case of swelling, redness, itching or any severe allergic reactions while using the product, discontinue use and consult with a specialist.

2) Do not apply on broken skin or wounded areas.

3) Precautions for storage and handling A) Keep out of reach of children. B) Store away from direct sunlight.

4) For external use only

DESCRIPTION

Uses:

Containing the UV suncare secret of Village 11 factory, this calming tone up sun block protects the skin from UV rays and external harm. Also, it helps to prevent sunburn.

Directions:

For the last step of your skin care, apply an appropriate amount onto areas of your skin that is exposed to sunlight.